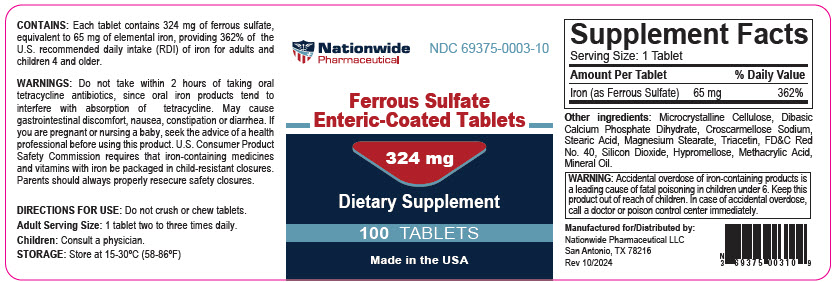 DRUG LABEL: Ferrous Sulfate 324mg Enteric Coated
NDC: 69375-003 | Form: TABLET, DELAYED RELEASE
Manufacturer: Nationwide Pharmaceutical, LLC
Category: other | Type: DIETARY SUPPLEMENT
Date: 20241011

ACTIVE INGREDIENTS: Ferrous Sulfate 65 mg/1 1
INACTIVE INGREDIENTS: MICROCRYSTALLINE CELLULOSE; DIBASIC CALCIUM PHOSPHATE DIHYDRATE; CROSCARMELLOSE SODIUM; STEARIC ACID; MAGNESIUM STEARATE; TRIACETIN; FD&C RED NO. 40; SILICON DIOXIDE; HYPROMELLOSE, UNSPECIFIED; METHACRYLIC ACID - METHYL METHACRYLATE COPOLYMER (1:1); MINERAL OIL

Ferrous Sulfate Enteric-Coated Tablets

CONTAINS

Each tablet contains 324 mg of ferrous sulfate, equivalent to 65 mg of elemental iron, providing 362% of the U.S. recommended daily intake (RDI) of iron for adults and children 4 and older.

WARNINGS

Do not take within 2 hours of taking oral tetracycline antibiotics, since oral iron products tend to interfere with absorption of tetracycline. May cause gastrointestinal discomfort, nausea, constipation or diarrhea. If you are pregnant or nursing a baby, seek the advice of a health professional before using this product. U.S. Consumer Product Safety Commission requires that iron-containing medicines and vitamins with iron be packaged in child-resistant closures. Parents should always properly resecure safety closures.

DIRECTIONS FOR USE

Do not crush or chew tablets.
Adult Serving Size: 1 tablet two to three times daily.
Children: Consult a physician.

STORAGE

Store at 15-30°C (58-86°F)

STATEMENT OF IDENTITY

Supplement Facts
Serving Size: 1 Tablet
Amount Per Tablet |  | % Daily Value
Iron (as Ferrous Sulfate) | 65 mg | 362%

Other ingredients: Microcrystalline Cellulose, Dibasic Calcium Phosphate Dihydrate, Croscarmellose Sodium, Stearic Acid, Magnesium Stearate, Triacetin, FD&C Red No. 40, Silicon Dioxide, Hypromellose, Methacrylic Acid, Mineral Oil.

SAFE HANDLING WARNING

WARNING: Accidental overdose of iron-containing products is a leading cause of fatal poisoning in children under 6. Keep this product out of reach of children. In case of accidental overdose, call a doctor or poison control center immediately.

HEALTH CLAIM

Manufactured for/Distributed by:
Nationwide Pharmaceutical LLC
San Antonio, TX 78216
Rev 10/2024

PRINCIPAL DISPLAY PANEL - 324 mg Tablet Bottle Label

Nationwide
Pharmaceutical

NDC 69375-0003-10

Ferrous Sulfate
Enteric-Coated Tablets

324 mg

Dietary Supplement

100 TABLETS

Made in the USA